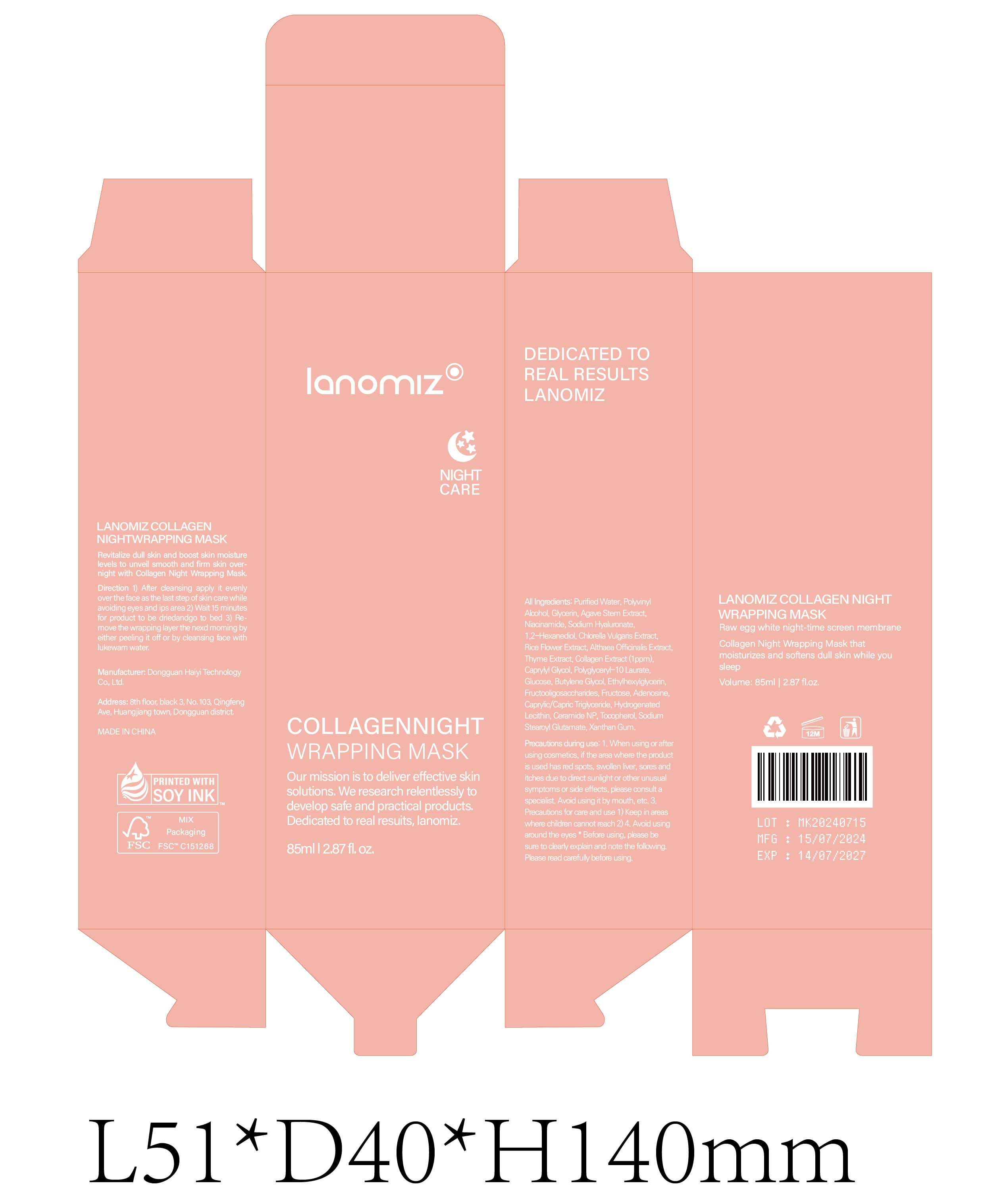 DRUG LABEL: LANOMIZ COLLAGEN NIGHTWRAPPING MASK
NDC: 84732-040 | Form: GEL
Manufacturer: Dongguan Haiyi Technology Co.,Ltd.
Category: otc | Type: HUMAN OTC DRUG LABEL
Date: 20241011

ACTIVE INGREDIENTS: ISOPROPYL PALMITATE 1 mg/100 mL
INACTIVE INGREDIENTS: ALMOND OIL; ALOE VERA LEAF; TEA TREE OIL; LINSEED OIL; UNDECYLENIC ACID; LAVENDER OIL; .ALPHA.-TOCOPHEROL ACETATE; WEST INDIAN LEMONGRASS OIL

Active ingredient

Isopropyl Palmitate

Inactive ingredient

Purified Water, PolyvinylAlcohol, Glycerin, Agave Stem Extract,Niacinamide, Sodium Hyaluronate,1,2-Hexanediol, Chlorella Vulgaris Extract,Rice Flower Extract, Althaea Officinalis Extract.Thyme Extract, Collagen Extract (1 ppm)Capryyl Glycol, Polyglyceryl-10 Laurate,Glucose, Butylene Glcol, Ethylhexylglycerin,Fructooligosaccharides, Fructose, Adenosine,Caprylic/Capric Trglyceride, HydrogenatedLecithin, Ceramide NP, Tocopherol, SodiumStearoyl Glutamate, Xanthan Gum.

Purpose section

Revitalize dull skin and boost skin moisturelevels to unveil smooth and firm skin over.night with Collagen Night Wrapping Mask.

Warning

1. When using or afterusing cosmetics, if the area where the productis used has red spots, swollen liver, sores anditches due to direct sunlight or other unusualsymptoms or side effects, please consult aspecialist, Avoid using it by mouth, etc.

3.Precautions for care and use1) Keep in areaswhere children cannot reach 2)

4. Avoid usingaround the eyes * Before using, please besure to clearty explain and note the followingPlease read carefully before using.

stop use

This product may cause allergic reactions in asmall number of people.
lf youexperience any discomfort,please stop using it immediately.

not use

Not suitable for use by children, pregnantor breast feeding people.

OUT OF CHILDREN

KEEP THE PRODUCT OUT OF REACH OF CHILDREN to

HOW TO USE

1) After cleansing apply it evenlyover the face as the last step of skin care whileavoiding eyes and ips area

2) Wait 15 minutesfor product to be driedandgo to bed

3) Re.move the wrapping layer the nexd moming byeither peeling it off or by cleansing face withlukewam water

Dosage

take an appropriateamount,Use 2-3 times a week